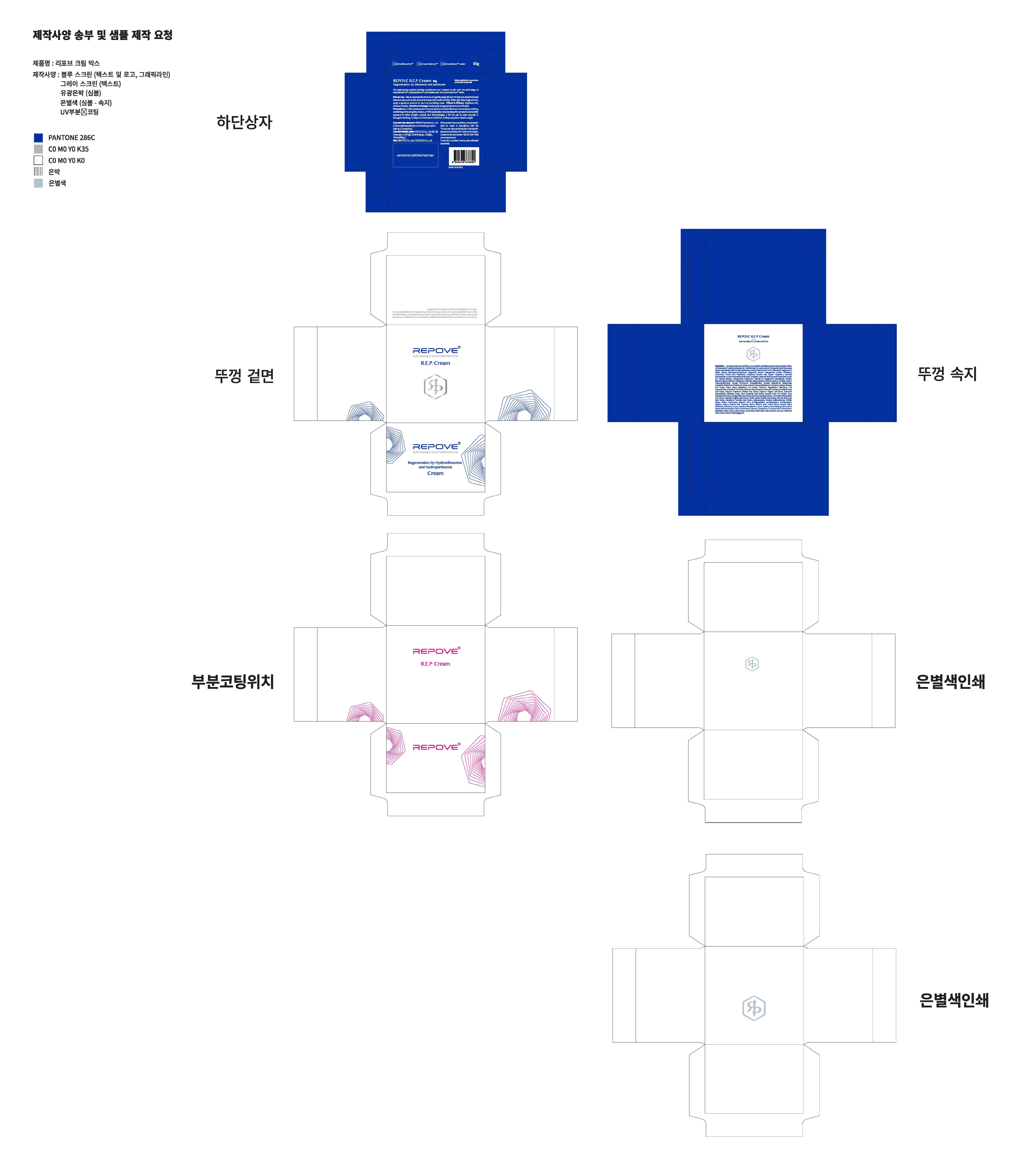 DRUG LABEL: REPOVE R.E.P
NDC: 73345-0030 | Form: CREAM
Manufacturer: Binotec Co., Ltd.
Category: otc | Type: HUMAN OTC DRUG LABEL
Date: 20190924

ACTIVE INGREDIENTS: GLYCERIN 4 g/100 g
INACTIVE INGREDIENTS: WATER; ADENOSINE

Drug Facts

ACTIVE INGREDIENT

Glycerin

INACTIVE INGREDIENT

Eucalyptus Globulus Leaf Water
Laurus Nobilis Leaf Water
Butylene Glycol
Water
1,2-Hexanediol
Propanediol
Macadamia Ternifolia Seed Oil
Simmondsia Chinensis (Jojoba) Seed Oil
Propylene Glycol Dibenzoate
Heptyl Undecylenate
Niacinamide
Cyclodextrin
Sorbitol
Rosa Canina Fruit Oil
Adenosine
Polyglyceryl-10 Oleate
Glyceryl Distearate
Caprylic/Capric Triglyceride
Alcohol
Hydrogenated lecithin
Cholesterol
Ubiquinone
Thioctic Acid
Glutathione
Tocopherol
Ascorbic Acid
Copper Tripeptide-1
Palmitoyl Pentapeptide-4
Acetyl Hexapeptide-8
Palmitoyl Tripeptide-5
Alanine/Histidine/Lysine Polypeptide Copper HCl
Cetearyl Stearate
Hydrogenated Polydecene
Trideceth-10
Polyglyceryl-3 Diisostearate
Sorbitan Stearate
Glyceryl Stearate
Polyglyceryl-2 Stearate
Stearyl Alcohol
Carbomer
Sodium Chloride
Sodium Polyacryloyldimethyl Taurate
Ammonium Acryloyldimethyltaurate/Beheneth-25 Methacrylate Crosspolymer
lanthus Emblica Fruit Extract
Rubus Fruticosus (Blackberry) Fruit Extract
Euterpe Oleracea Fruit Extract
Rubus Idaeus (Raspberry) Fruit Extract
ium Angustifolium (Blueberry) Fruit Extract
Vaccinium Myrtillus Fruit Extract
Vaccinium Macrocarpon (Cranberry) Fruit Extract
Camellia Sinensis Leaf Extract
Solanum Tuberosum (Potato) Pulp Extract
Origanum Vulgare Leaf Extract
Mentha Viridis (Spearmint) Extract
Melissa Officinalis Extract
Pinus Koraiensis Seed Extract
Hovenia Dulcis Fruit Extract
Thuja Orientalis Seed Extract
Ginkgo Biloba Nut Extract
Myrciaria Dubia Seed Extract
Terminalia Ferdinandiana Fruit Extract
Adansonia Digitata Seed Extract
Coffea Arabica (Coffee) Seed Extract
Aleurites Moluccana Seed Extract
Macadamia Ternifolia Seed Extract
Madecassoside
Dimethyl Sulfone
Morinda Citrifolia Extract
Sodium Hyaluronate
Disodium EDTA
sh-Oligopeptide-1
sh-Polypeptide-1
sh-Polypeptide-3
Histidine
Arginine
Aspartic Acid
Threonine
Serine
Glutamic Acid
Proline
Glycine
Alanine
Valine
Methionine
Isoleucine
Leucine
Tyrosine
Phenylalanine
Lysine
Cysteine
Panax Ginseng Callus Culture Extract
Nelumbo Nucifera Callus Culture Extract
Solanum Lycopersicum (Tomato) Callus Culture Extract
Neofinetia Falcata Callus Culture Extract
Oryza Sativa (Rice) Callus Culture Extract
Ipomoea Hederacea Callus Culture Extract
Ethylhexylglycerin

PURPOSE

Skin protectant

keep out of reach of the children

INDICATIONS AND USAGE

Depending on the skin type, take an appropriate amount with the enclosed spatula and apply on the face.

DOSAGE AND ADMINISTRATION

for external use only

WARNINGS

If skin shows the following reactions while using 3G AB_Solution, reduce the amount of use drastically or discontinue use.

1. If itching continues for 7-10 days

2. If skin experiences a burning sensation or becomes reddish (dry skin type, particularly extremely dry skin)

3. If dead skin cells are generated drastically

* If you are receiving skin treatment due to skin diseases consult your doctor before use.